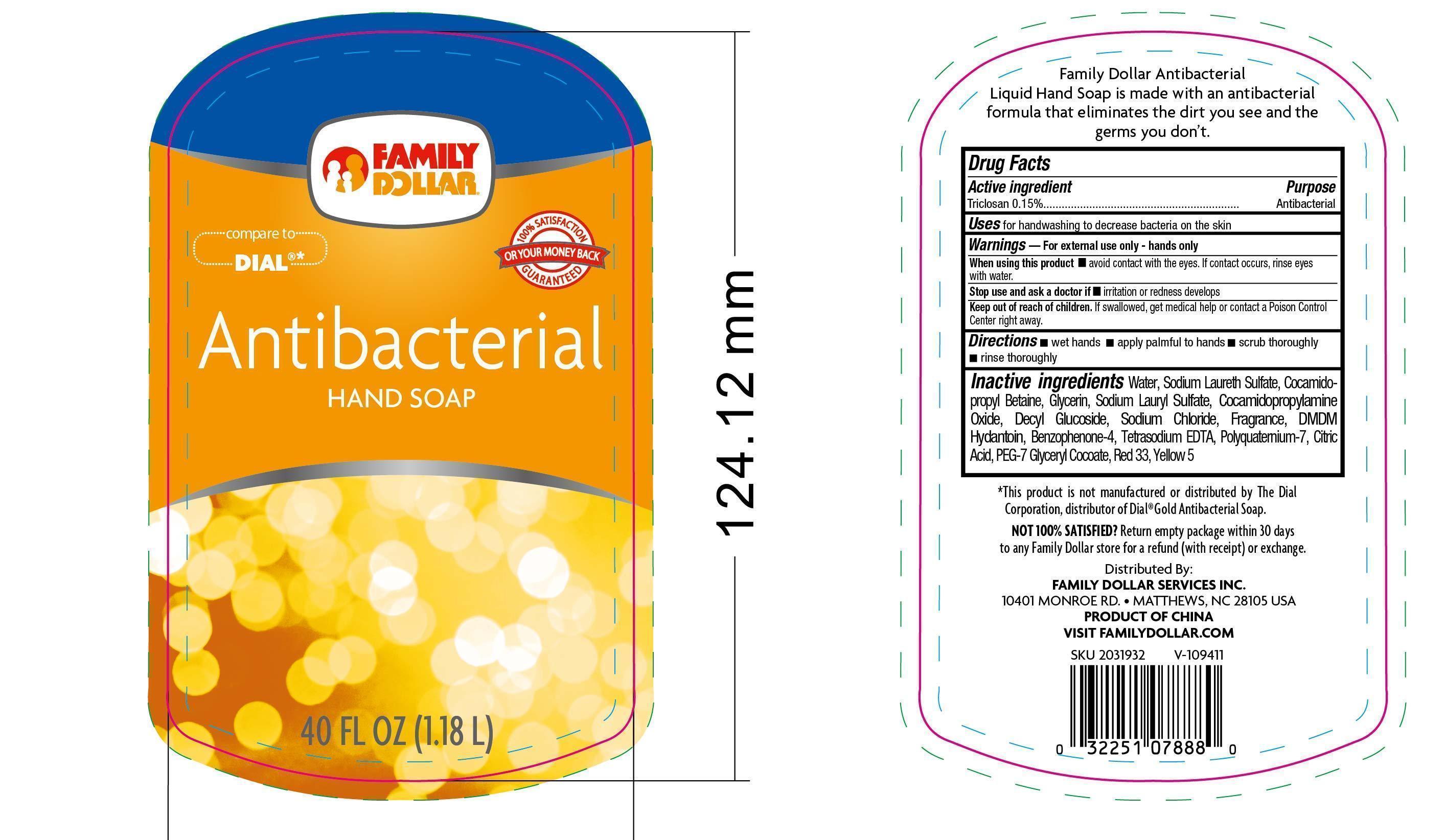 DRUG LABEL: Family Dollar Antibacterial Hand
NDC: 55319-512 | Form: SOAP
Manufacturer: Family Dollar Services Inc.
Category: otc | Type: HUMAN OTC DRUG LABEL
Date: 20140102

ACTIVE INGREDIENTS: TRICLOSAN 0.15 g/100 mL
INACTIVE INGREDIENTS: WATER; SODIUM LAURETH SULFATE; COCAMIDOPROPYL BETAINE; SODIUM CHLORIDE; GLYCERIN; SODIUM LAURYL SULFATE; COCAMIDOPROPYLAMINE OXIDE; DECYL GLUCOSIDE; DMDM HYDANTOIN; FD&C YELLOW NO. 5; D&C RED NO. 33

Drug Facts

Active Ingredient

Triclosan 0.15%

Purpose

Antibacterial

Uses

• for hand washing to decrease bacteria on the skin.

Warnings

• For external use only

- hands only

When using this product

• avoid contact with the eyes, if contact occurs, rinse eyes with water.

Stop use and ask a doctor if

irritation or redness develops.

Keep out of the reach of children

If swallowed, get medical help or contact a Poison Control Center right away.

Directions

•wet hands • apply palmful to hands • scrub thoroughly • rinse thoroughly

Inactive ingredients

water, sodium laureth sulfate, cocamidopropyl betaine, sodium chloride, cocamide DEA, glycerin, fragrance, Cocamidopropylamine Oxide, Decyl Glucoside, Po;yquatemium-7, methylisothiazolinone, tetrasodium EDTA, citric acid, benzophenone-4, FDC yellow no. 5, DC red no. 33